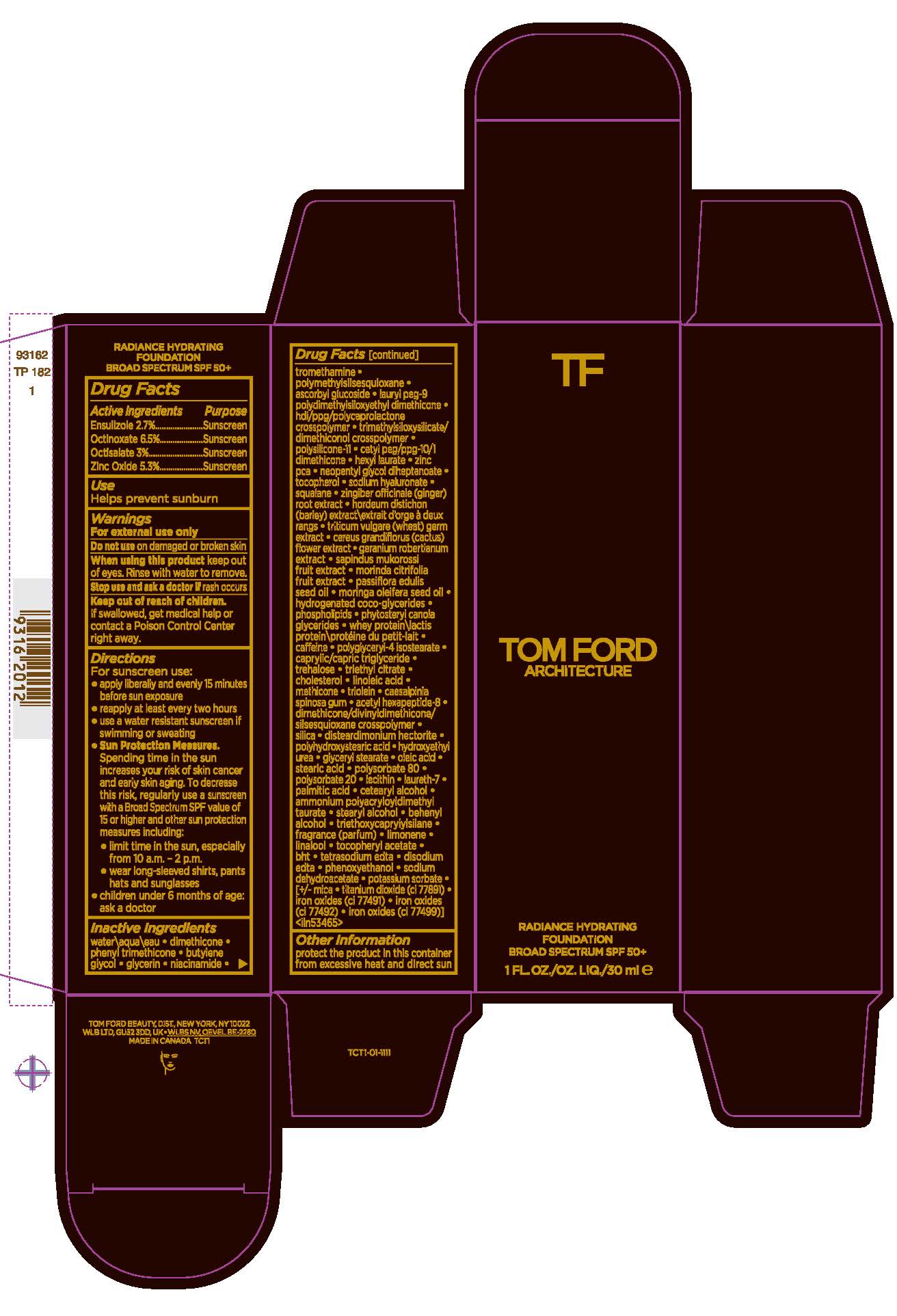 DRUG LABEL: TOM FORD ARCHITECTURE RADIANCE HYDRATING FOUNDATION BROAD SPECTRUM SPF 50
NDC: 76398-015 | Form: EMULSION
Manufacturer: TOM FORD BEAUTY DIST
Category: otc | Type: HUMAN OTC DRUG LABEL
Date: 20241206

ACTIVE INGREDIENTS: OCTINOXATE 65 mg/1 mL; OCTISALATE 30 mg/1 mL; ZINC OXIDE 53 mg/1 mL; ENSULIZOLE 27 mg/1 mL
INACTIVE INGREDIENTS: ZINGIBER OFFICINALE (GINGER) ROOT EXTRACT; CAFFEINE; OLEIC ACID; LIMONENE, (+)-; TETRASODIUM EDTA; PHENOXYETHANOL; CI 77492; BUTYLENE GLYCOL; DIMETHICONE/VINYL DIMETHICONE CROSSPOLYMER (SOFT PARTICLE); TOCOPHEROL; SQUALANE; WHEY; TREHALOSE; GLYCERYL STEARATE; POLYSORBATE 80; LAURETH-7; CI 77499; NEOPENTYL GLYCOL DIHEPTANOATE; PASSIFLORA EDULIS SEED OIL; MORINGA OLEIFERA SEED OIL; CAPRYLIC/CAPRIC TRIGLYCERIDE; CAESALPINIA SPINOSA GUM; POLYSORBATE 20; GLYCERIN; HEXYL LAURATE; ZINC PCA; SODIUM HYALURONATE; GERANIUM ROBERTIANUM EXTRACT; METHICONE (20 CST); DIMETHICONE/DIVINYLDIMETHICONE/SILSESQUIOXANE CROSSPOLYMER; HYDROXYETHYL UREA; ALPHA-TOCOPHEROL ACETATE; EDETATE DISODIUM ANHYDROUS; SODIUM DEHYDROACETATE; MICA; SAPINDUS MUKOROSSI FRUIT; CETEARYL ALCOHOL; WATER; PHENYL TRIMETHICONE; ASCORBYL GLUCOSIDE; LAURYL PEG-9 POLYDIMETHYLSILOXYETHYL DIMETHICONE; SELENICEREUS GRANDIFLORUS FLOWER; MORINDA CITRIFOLIA FRUIT; HYDROGENATED COCO-GLYCERIDES; TRIETHYL CITRATE; SILICA; PALMITIC ACID; BEHENYL ALCOHOL; SOYBEAN LECITHIN; POLYGLYCERYL-4 ISOSTEARATE; CHOLESTEROL; LINOLEIC ACID; TRIOLEIN; ACETYL HEXAPEPTIDE-8; TRIETHOXYCAPRYLYLSILANE; LINALOOL; BHT; POTASSIUM SORBATE; CI 77891; POLYMETHYLSILSESQUIOXANE; DIMETHICONE; NIACINAMIDE; TROMETHAMINE; CETYL PEG/PPG-10/1 DIMETHICONE (HLB 5); HORDEUM DISTICHON (BARLEY) EXTRACT; TRITICUM VULGARE (WHEAT) GERM; DISTEARDIMONIUM HECTORITE; POLYHYDROXYSTEARIC ACID (2300 MW); STEARIC ACID; AMMONIUM POLYACRYLOYLDIMETHYL TAURATE; STEARYL ALCOHOL; CI 77491

TOM FORD ARCHITECTURE RADIANCE HYDRATING FOUNDATION BROAD SPECTRUM SPF 50+

Active Ingredients

ENSULIZOLE 2.7%
OCTINOXATE 6.5%
OCTISALATE 3%
ZINC OXIDE 5.3%

Purpose

Sunscreen

USE

helps prevent sunburn

Warnings

For external use only

Do not use

on damaged or broken skin

When using this product

keep out of eyes. Rinse with water to remove.

Stop use and ask a doctor if

rash occurs

Keep out of reach of children.

If product is swallowed, get medical help or contact a Poison Control Center right away.

Directions

For sunscreen use:
apply liberally 15 minutes before sun exposure
reapply at least every two hours
use a water resistant sunscreen if swimming or sweating
Sun Protection Measures. Spending time in the sun increases your risk of skin cancer and early skin aging. To decrease this risk, regularly use a sunscreen with a Broad Spectrum SPF value of 15 or higher and other sun protection measures including:
limit time in the sun, especially from 10 a.m.–2 p.m.
wear long-sleeved shirts, pants, hats and sunglasses
children under 6 months of age: ask a doctor

Inactive Ingredients

WATER\AQUA\EAU,DIMETHICONE,PHENYL TRIMETHICONE,BUTYLENE GLYCOL,GLYCERIN,NIACINAMIDE,TROMETHAMINE,POLYMETHYLSILSESQUIOXANE,ASCORBYL GLUCOSIDE,LAURYL PEG-9 POLYDIMETHYLSILOXYETHYL DIMETHICONE,HDI/PPG/POLYCAPROLACTONE CROSSPOLYMER,TRIMETHYLSILOXYSILICATE/DIMETHICONOL CROSSPOLYMER,POLYSILICONE-11,CETYL PEG/PPG-10/1 DIMETHICONE,HEXYL LAURATE,ZINC PCA,NEOPENTYL GLYCOL DIHEPTANOATE,TOCOPHEROL,SODIUM HYALURONATE,SQUALANE,ZINGIBER OFFICINALE (GINGER) ROOT EXTRACT,HORDEUM DISTICHON (BARLEY) EXTRACT\EXTRAIT D'ORGE À DEUX RANGS,TRITICUM VULGARE (WHEAT) GERM EXTRACT,CEREUS GRANDIFLORUS (CACTUS) FLOWER EXTRACT,GERANIUM ROBERTIANUM EXTRACT,SAPINDUS MUKOROSSI FRUIT EXTRACT,MORINDA CITRIFOLIA FRUIT EXTRACT,PASSIFLORA EDULIS SEED OIL,MORINGA OLEIFERA SEED OIL,HYDROGENATED COCO-GLYCERIDES,PHOSPHOLIPIDS,PHYTOSTERYL CANOLA GLYCERIDES,WHEY PROTEIN\LACTIS PROTEIN\PROTÉINE DU PETIT-LAIT,CAFFEINE,POLYGLYCERYL-4 ISOSTEARATE,CAPRYLIC/CAPRIC TRIGLYCERIDE,TREHALOSE,TRIETHYL CITRATE,CHOLESTEROL,LINOLEIC ACID,METHICONE,TRIOLEIN,CAESALPINIA SPINOSA GUM,ACETYL HEXAPEPTIDE-8,DIMETHICONE/DIVINYLDIMETHICONE/SILSESQUIOXANE CROSSPOLYMER,SILICA,DISTEARDIMONIUM HECTORITE,POLYHYDROXYSTEARIC ACID,HYDROXYETHYL UREA,GLYCERYL STEARATE,OLEIC ACID,STEARIC ACID,POLYSORBATE 80,POLYSORBATE 20,LECITHIN,LAURETH-7,PALMITIC ACID,CETEARYL ALCOHOL,AMMONIUM POLYACRYLOYLDIMETHYL TAURATE,STEARYL ALCOHOL,BEHENYL ALCOHOL,TRIETHOXYCAPRYLYLSILANE,FRAGRANCE (PARFUM),LIMONENE,LINALOOL,TOCOPHERYL ACETATE,BHT,TETRASODIUM EDTA,DISODIUM EDTA,PHENOXYETHANOL,SODIUM DEHYDROACETATE,POTASSIUM SORBATE, [+/- MICA,TITANIUM DIOXIDE (CI 77891),IRON OXIDES (CI 77491),IRON OXIDES (CI 77492),IRON OXIDES (CI 77499)] <ILN53465>

Other information

protect the product in this container from excessive heat and direct sun

PDP

TOM FORD

ARCHITECTURE

RADIANCE HYDRATING

FOUNDATION

BROAD SPECTRUM SPF 50+

1 FL.OZ/OZ. LIQ/30ml e